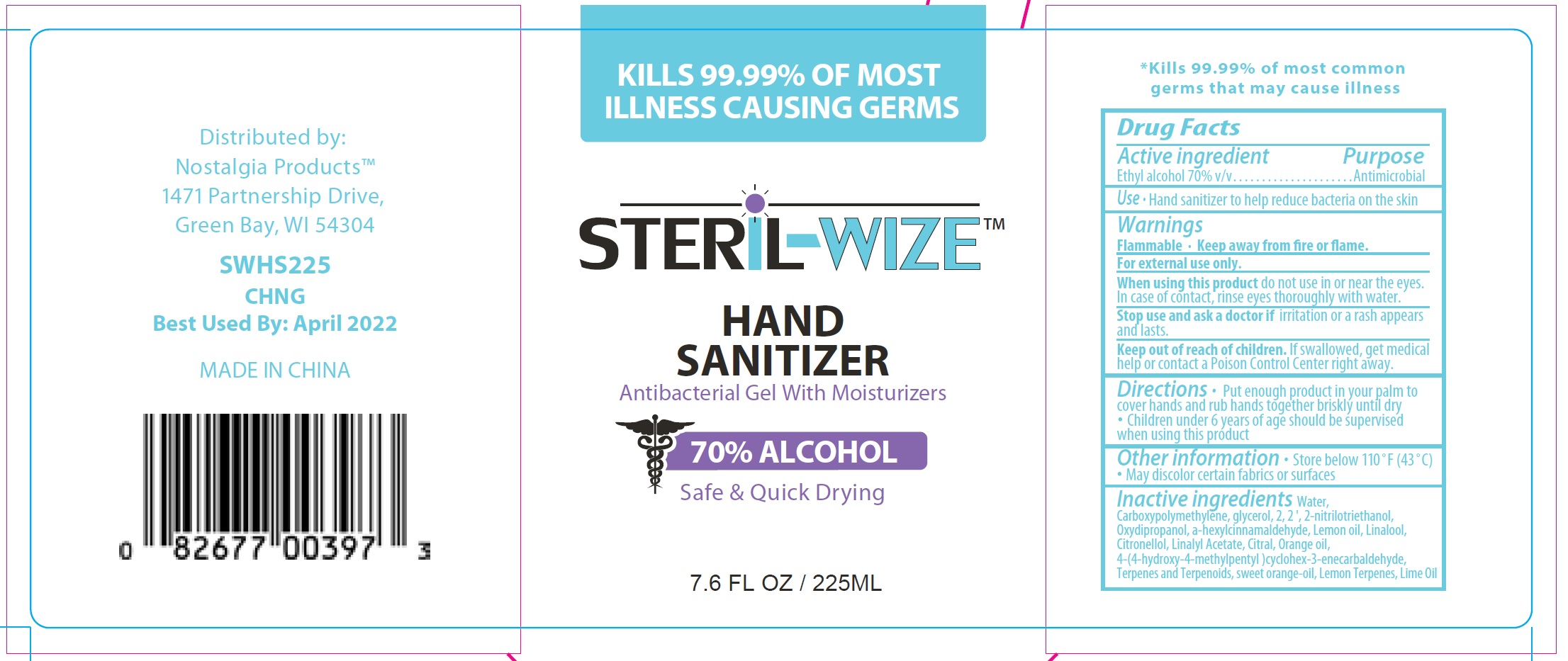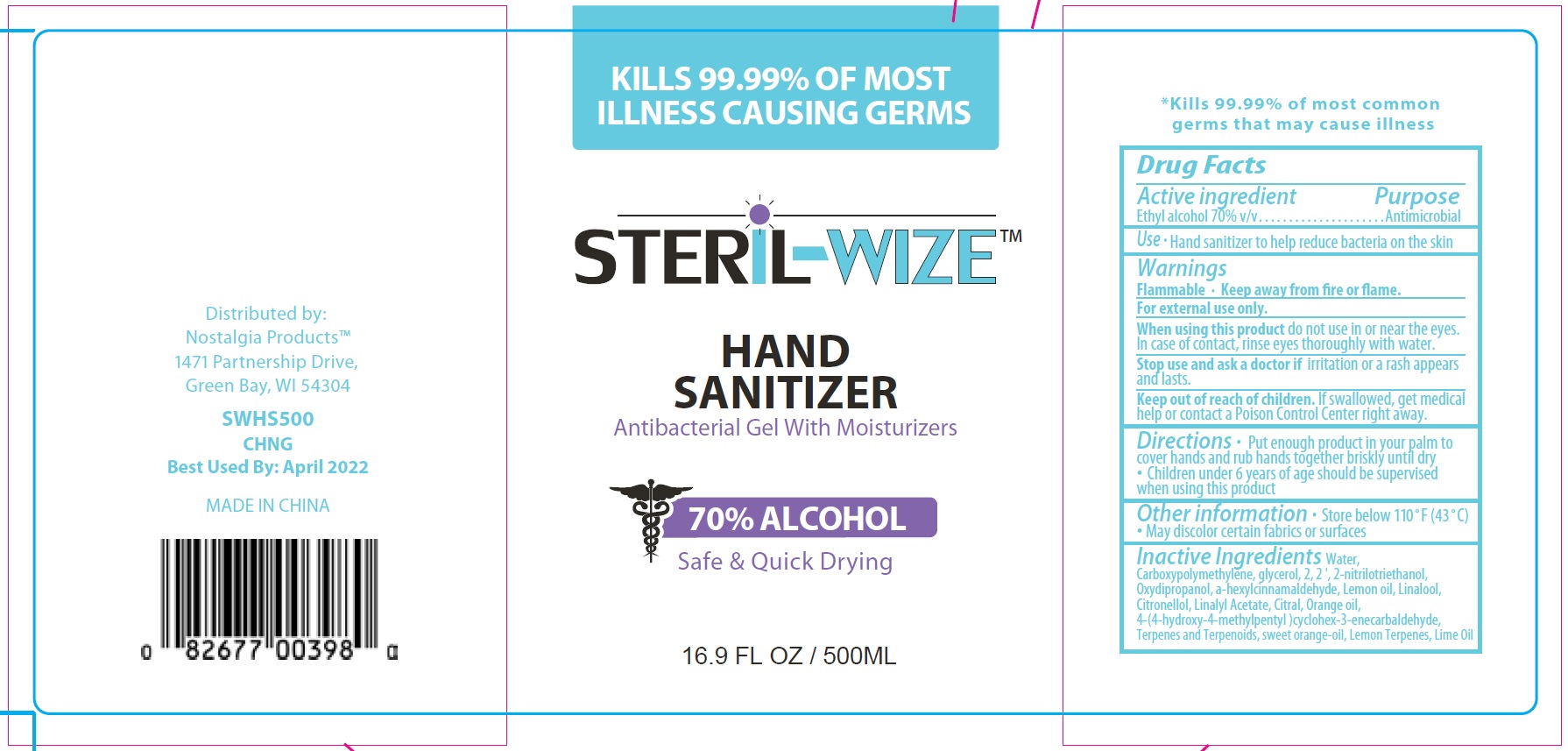 DRUG LABEL: Steril Wize Hand Sanitizer
NDC: 77051-000 | Form: GEL
Manufacturer: Nostalgia Products LLC
Category: otc | Type: HUMAN OTC DRUG LABEL
Date: 20200506

ACTIVE INGREDIENTS: ALCOHOL 0.7 mL/1 mL
INACTIVE INGREDIENTS: .ALPHA.-HEXYLCINNAMALDEHYDE; HYDROXYISOHEXYL 3-CYCLOHEXENE CARBOXALDEHYDE; WATER; CARBOXYPOLYMETHYLENE; GLYCERIN; TROLAMINE; LEMON OIL; LINALOOL, (+/-)-; .BETA.-CITRONELLOL, (R)-; LINALYL ACETATE; CITRAL; ORANGE OIL; LEMON; LIME OIL

Steril-Wize Hand Sanitizer

Active ingredient

Ethyl alcohol 70% v/v

Purpose

Antimicrobial

Use

- Hand sanitizer to help reduce bacteria on the skin

Warnings

Flammable. Keep away from fire or flame.

For external use only.

When using this product

do not use in or near the eyes. In case of contact, rinse eyes thoroughly with water.

Stop use and ask a doctor

if irritation or a rash appears and lasts.

Keep out of reach of children.

If swallowed, get medical help or contact a Poison Control Center right away.

Directions

- Put enough product in your palm to cover hands and rub hands together briskly until dry
- Children under 6 years of age should be supervised when using this product

Other information

- Store below 110°F (43°C)
- May discolor certain fabrics or surfaces

Inactive ingredients

Water, Carboxypolymethylene, glycerol, 2, 2 ', 2-nitrilotriethanol, Oxydipropanol, a-hexylcinnamaldehyde, Lemon oil, Linalool, Citronellol, Linalyl Acetate, Citral, Orange oil, 4-(4-hydroxy-4-methylpentyl)cyclohex-3-enecarbaldehyde, Terpenes and Terpenoids, sweet orange-oil, Lemon Terpenes, Lime Oil